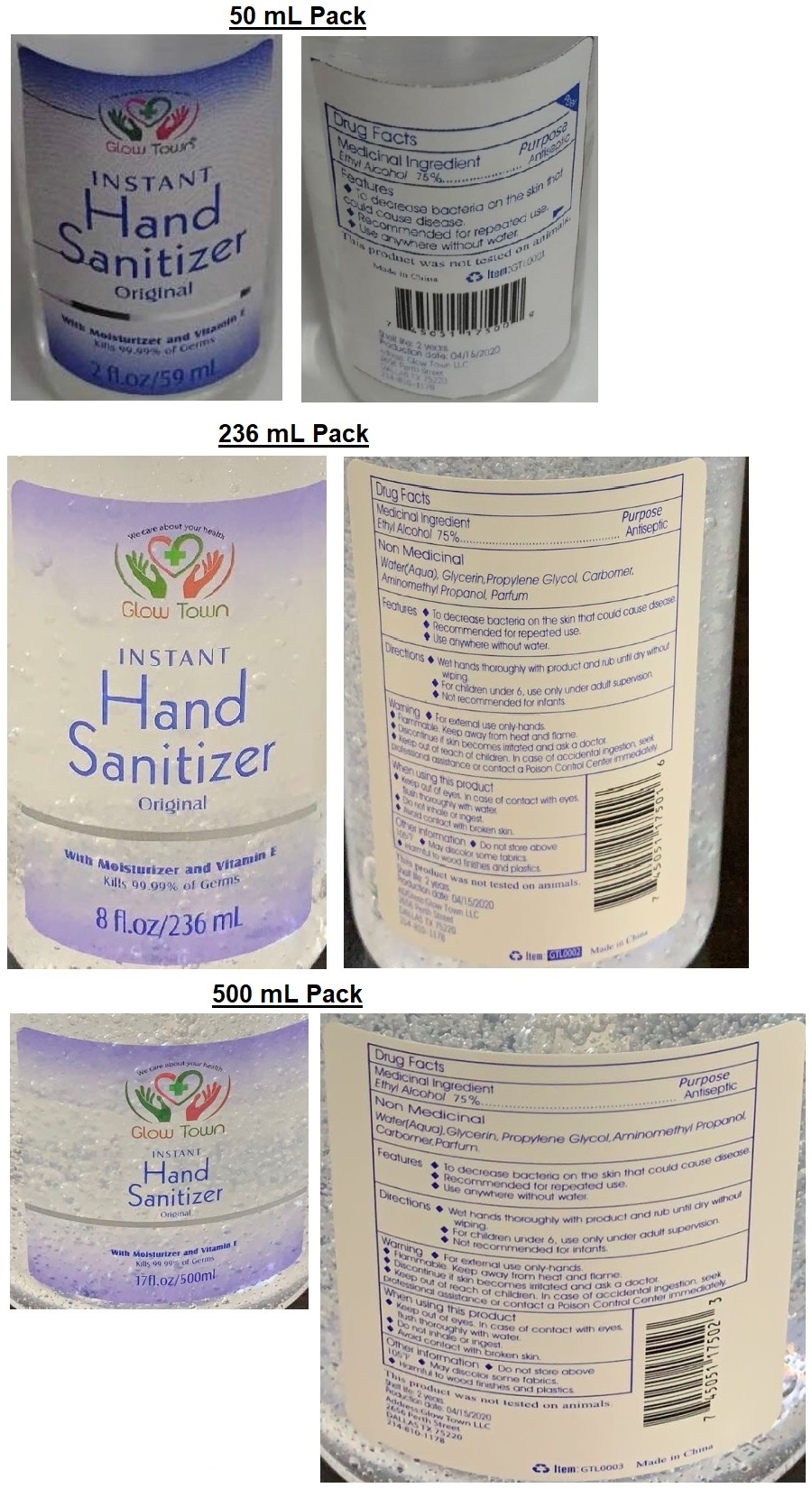 DRUG LABEL: Glow Town
NDC: 75047-186 | Form: LIQUID
Manufacturer: Glow Town Llc
Category: otc | Type: HUMAN OTC DRUG LABEL
Date: 20200429

ACTIVE INGREDIENTS: ALCOHOL 75 mL/100 mL
INACTIVE INGREDIENTS: WATER; GLYCERIN; PROPYLENE GLYCOL; CARBOMER HOMOPOLYMER, UNSPECIFIED TYPE; AMINOMETHYLPROPANOL

Glow Town INSTANT Hand Sanitizer Original

Medicinal Ingredient

Ethyl Alcohol 75%

Purpose

Antiseptic

Non Medicinal

Water(Aqua), Glycerin, Propylene Glycol, Carbomer, Aminomethyl Propanol, Parfum

INDICATIONS AND USAGE

Features ♦ To decrease bacteria on the skin that could cause disease.

♦ Recommended for repeated use.

♦ Use anywhere without water.

DOSAGE AND ADMINISTRATION

Directions ♦ Wet hands thoroughly with product and rub until dry without wiping.

♦ For children under 6, use only under adult supervision.

♦ Not recommended for infants.

WARNINGS

Warning ♦ For external use only-hands.

♦ Flammable. Keep away from heat and flame.

♦ Discontinue if skin becomes irritated and ask a doctor.

When using this product

♦ Keep out of eyes. In case of contact with eyes, flush thoroughly with water.

♦ Do not inhale or ingest.

♦ Avoid contact with broken skin.

♦ Keep out of reach of children. In case of accidental ingestion, seek professional assistance or contact a Poison Control Center immediately.

Other Information ♦ Do not store above 105°F ♦ May discolour some fabrics.

♦ Harmful to wood finishes and plastics.

With Moisturizer and Vitamin E

Kills 99.99% of Germs

This product was not tested on animals.

Shelf life: 2 years

Production date: 04/15/2020

Address: Glow Town LLC

2656 Perth Street

DALLAS TX 25220

214-610-1178

Made in China